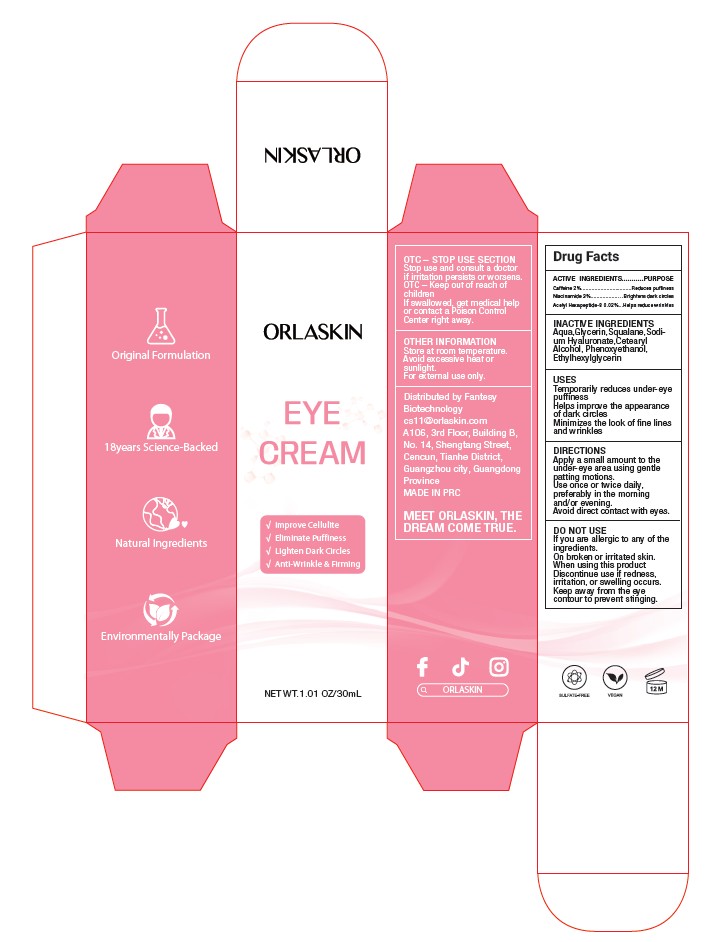 DRUG LABEL: Anti-wrinkle  eye cream
NDC: 84356-005 | Form: CREAM
Manufacturer: Guangzhou Yapeng Refinement Chemical Co., Ltd.
Category: otc | Type: HUMAN OTC DRUG LABEL
Date: 20250619

ACTIVE INGREDIENTS: CAFFEINE 2 g/100 mL; ACETYL HEXAPEPTIDE-8 0.02 g/100 mL; NIACINAMIDE 3 g/100 mL
INACTIVE INGREDIENTS: SQUALANE; SODIUM HYALURONATE; ETHYLHEXYLGLYCERIN; GLYCERIN; AQUA; CETEARYL ALCOHOL; PHENOXYETHANOL

INDICATIONS AND USAGE

Temporarily reduces under-eye puffiness
Helps improve the appearance of dark circles
Minimizes the look of fine lines and wrinkles

Stop use and consult a doctor if irritation persists or worsens.

DO NOT USE

If you are allergic to any of the ingredients.
On broken or irritated skin.
When using this product Discontinue use if redness,irritation, or swelling occurs.
Keep away from the eye contour to prevent stinging.

Keep out of reach of children,The above warning signs have been listed in the labels

PURPOSE

Temporarily reduces under-eye puffiness
Helps improve the appearance of dark circles
Minimizes the look of fine lines and wrinkles

DOSAGE AND ADMINISTRATION

Apply a small amount to the under-eye area using gentle patting motions.
Use once or twice daily,preferably in the morning and/or evening.
Avoid direct contact with eyes.

WARNINGS

Do not take orally. If swallowed, get medical help or contact a Poison Control Center right away.

INACTIVE INGREDIENT

Aqua,Glycerin,Squalane,Sodium Hyaluronate,Cetearyl
Alcohol, Phenoxyethanol, Ethylhexylglycerin